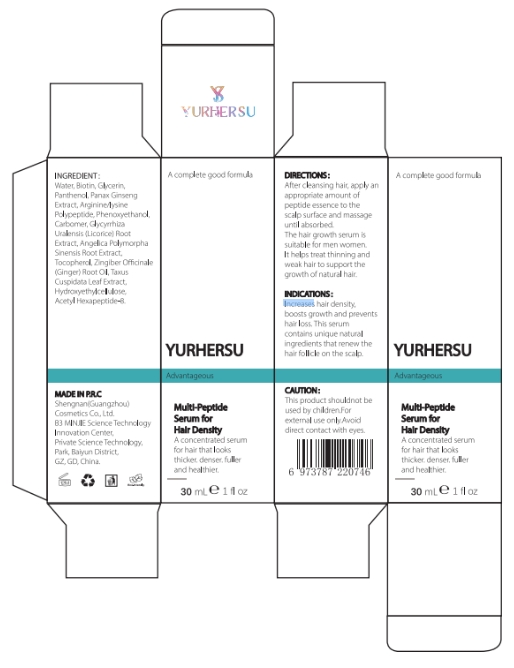 DRUG LABEL: Multi-Peptide Serum for Hair Density
NDC: 84019-010 | Form: LIQUID
Manufacturer: Shengnan (Guangzhou) Cosmetics Co., LTD
Category: otc | Type: HUMAN OTC DRUG LABEL
Date: 20241118

ACTIVE INGREDIENTS: BIOTIN 100 mg/1 mL
INACTIVE INGREDIENTS: PHENOXYETHANOL; ACETYL HEXAPEPTIDE-8; ZINGIBER OFFICINALE (GINGER) ROOT OIL; WATER; HYDROXYETHYLCELLULOSE; PANTHENOL; TOCOPHEROL; CARBOMER; GLYCERIN

Multi-Peptide Serum for Hair Density

PURPOSE

Increases hair density,boosts growth and preventshair loss.

WARNINGS

This product shouldnot beused by children.Forexternal use only.Avoiddirect contact with eyes.

Stop use and ask doctor if rash occurs.

ACTIVE INGREDIENT

Biotin

WHEN USING

Do not apply to wounds or damaged skin.

INACTIVE INGREDIENT

Water

Glycerin
Panthenol
Panax Ginseng Extract
Arginine/lysine Polypeptide
Phenoxyethanol
Carbomer
Glycyrrhiza Uralensis (Licorice) Root Extract
Angelica Polymorpha Sinensis Root Extract
Tocopherol
Zingiber Officinale (Ginger) Root Oil
Taxus Cuspidata Leaf Extract
Hydroxyethylcellulose
Acetyl Hexapeptide-8

DOSAGE AND ADMINISTRATION

Apply 1-2 times a day

INDICATIONS AND USAGE

After cleansing hair, apply anappropriate amount ofpeptide essence to thescalp surface and massageuntil absorbed.